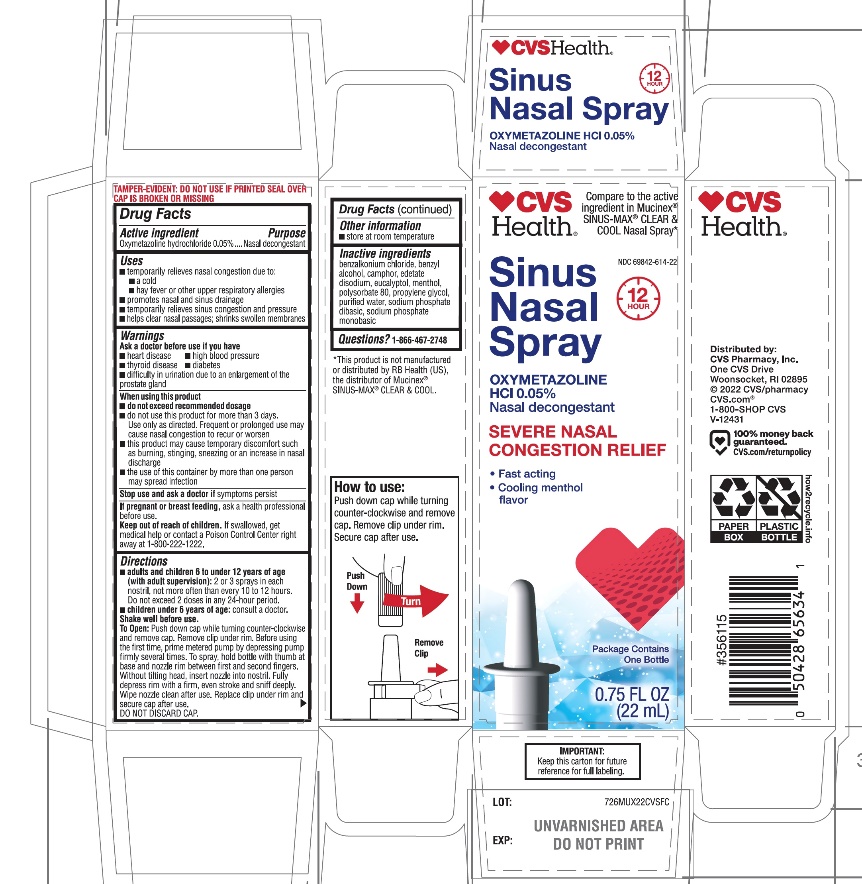 DRUG LABEL: CVS Severe Nasal Congestion Relief

NDC: 69842-614 | Form: SPRAY
Manufacturer: CVS PHARMACY, INC.
Category: otc | Type: HUMAN OTC DRUG LABEL
Date: 20251209

ACTIVE INGREDIENTS: OXYMETAZOLINE HYDROCHLORIDE 0.05 g/100 mL
INACTIVE INGREDIENTS: BENZALKONIUM CHLORIDE; BENZYL ALCOHOL; CAMPHOR (NATURAL); EDETATE DISODIUM; EUCALYPTOL; MENTHOL, UNSPECIFIED FORM; POLYSORBATE 80; POLYETHYLENE GLYCOL, UNSPECIFIED; PROPYLENE GLYCOL; WATER; SODIUM PHOSPHATE, DIBASIC, UNSPECIFIED FORM; SODIUM PHOSPHATE, MONOBASIC, UNSPECIFIED FORM

NASAL SPRAY SEVERE NASAL CONGESTION RELIEF

Drug Facts

Active ingredient

Oxymetazoline hydrochloride 0.05%

Purpose

Nasal decongestant

Uses

- temporarily relieves nasal congestion due to:
  - a cold
  - hay fever or other upper respiratory allergies
- promotes nasal and sinus drainage
- temporarily relieves sinus congestion and pressure
- helps clear nasal passages; shrinks swollen membranes

Warnings

Ask a doctor before use if you have

- heart disease
- high blood pressure
- thyroid disease
- diabetes
- difficulty in urination due to enlargement of the prostate gland

When using this product

- do not exceed recommended dosage
- do not use this product for more than 3 days. Use only as directed. Frequent or prolonged use may cause nasal congestion to recur or worsen
- this product may cause temporary discomfort such as burning, stinging, sneezing, or an increase in nasal discharge
- the use of this container by more than one person may spread infection

Stop use and ask a doctor ifsymptoms persist

PREGNANCY OR BREAST FEEDING

If pregnant or breast-feeding,ask a health professional before use.

Keep out of reach of children.If swallowed, get medical help or contact a Poison Control Center right away at 1-800-222-1222.

Directions

- adults and children 6 to under 12 years of age (with adult supervision):2 or 3 sprays in each nostril, not more often than every 10 to 12 hours. Do not exceed 2 doses in any 24-hour period.
- children under 6 years of age:consult a doctor.

Shake well before use.

To open:Push down cap while turning counter-clockwise and remove cap. Remove clip under rim. Before using for the first time, prime metered pump by depressing firmly several times. To spray, hold bottle with thumb at the base and nozzle between first and second fingers. Without tilting head, insert nozzle into nostril. Fully depress pump all the way down with a firm even stroke and sniff deeply. Wipe nozzle clean after use.

DO NOT DISCARD CAP.

Other information

- store at room temperature

Inactive ingredients

benzalkonium chloride, benzyl alcohol, camphor, edetate disodium, eucalyptol, menthol, polysorbate 80, propylene glycol, purified water, sodium phosphate dibasic, sodium phosphate monobasic.

Questions?

1-866-467-2748

PRINCIPAL DISPLAY PANEL - 22 mL Bottle Carton

*Compare to the active ingredient in Mucinex® SINUS-MAX® CLEAR & COOL Nasal Spray

NDC 69842-614-22

NASAL SPRAY
Oxymetazoline HCl 0.05%
Nasal Decongestant

SEVERE NASAL CONGESTION RELIEF

CLEAR & COOL

- Fast acting
- Lasts 12 Hours
- Cooling Menthol
  flavor

3/4 FL OZ (22 mL)

IMPORTANT: Keep this carton for future reference for full labeling.

Distributed By: